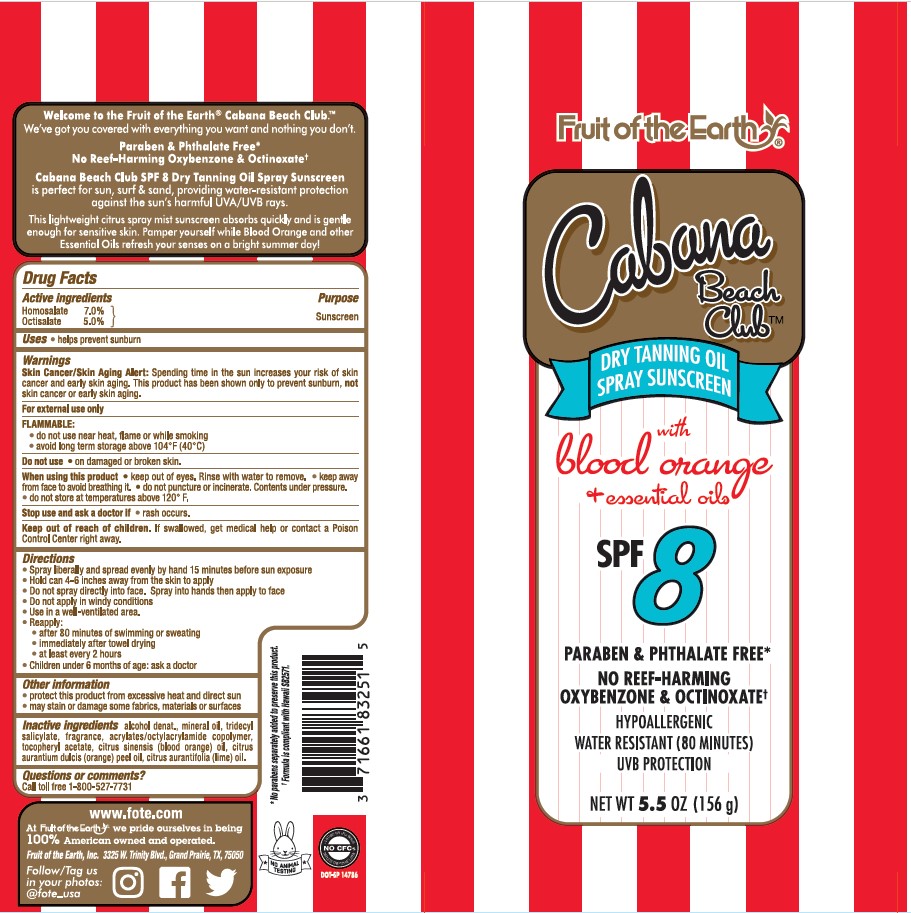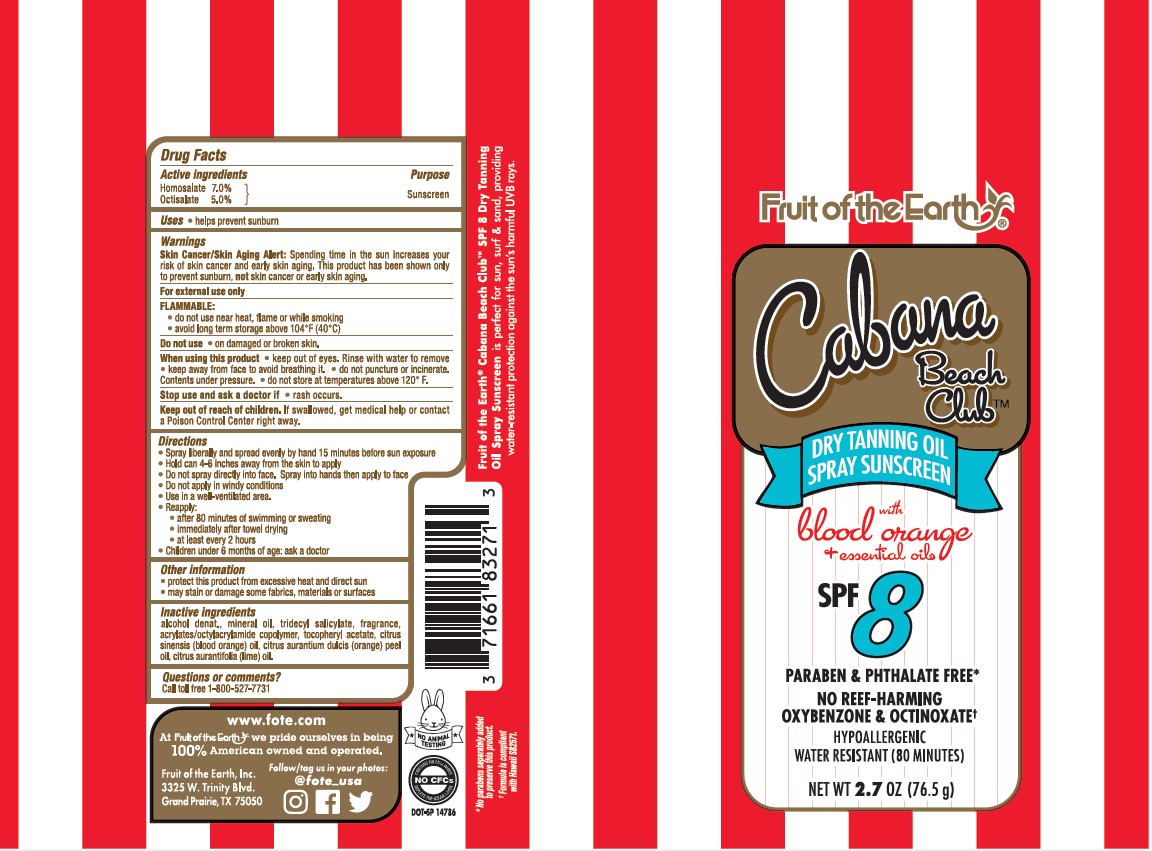 DRUG LABEL: FOTE CABANA BEACH CLUB WITH BLOOD ORANGE AND ESSENTIAL OILS SPF 8 DRY TANNING SUNSCREEN
NDC: 62217-043 | Form: AEROSOL, SPRAY
Manufacturer: FRUIT OF THE EARTH, INC.
Category: otc | Type: HUMAN OTC DRUG LABEL
Date: 20241017

ACTIVE INGREDIENTS: HOMOSALATE 70 mg/1 g; OCTISALATE 50 mg/1 g
INACTIVE INGREDIENTS: ALCOHOL; MINERAL OIL; TRIDECYL SALICYLATE; ACRYLATE/ISOBUTYL METHACRYLATE/N-TERT-OCTYLACRYLAMIDE COPOLYMER (75000 MW); LIME OIL; ORANGE OIL; .ALPHA.-TOCOPHEROL ACETATE

FRUIT OF THE EARTH CABANA BEACH CLUB WITH BLOOD ORANGE & ESSENTIAL OILS SPF 8 DRY TANNING OIL SPRAY SUNSCREEN

Active ingredients

Homosalate 7.0%, Octisalate 5.0%

Purpose

Sunscreen

Uses

- helps prevent sunburn

Warnings

Skin Cancer/Skin Aging Alert: Spending time in the sun increases your risk of skin cancer and early skin aging. This product has been shown only to prevent sunburn, not skin cancer or early skin aging.

FLAMMABLE:

- do not use near heat, flame or while smoking
- avoid long term storage above 104°F (40°C)

Do not use

• on damaged or broken skin.

When using this product

• keep out of eyes. Rinse with water to remove • keep away from face to avoid breathing it. • do not puncture or incinerate. Contents under pressure. • do not store at temperatures above 120°F.

Stop use and ask a doctor if

• rash occurs.

Keep out of reach of children.

If swallowed, get medical help or contact a Poison Control Center right away.

Directions

- Spray liberally and spread evenly by hand 15 minutes before sun exposure
- Hold can 4-6 inches away from the skin to apply
- Do not spray directly into face. Spray into hands then apply to face
- Do not apply in windy conditions
- Use in a well-ventilated area.
- Reapply:

• after 80 minutes of swimming or sweating

• immediately after towel drying

• at least every 2 hours

- Children under 6 months of age: Ask a doctor

Other information

- protect the product in this container from excessive heat and direct sun
- may stain or damage some fabrics, materials or surfaces

Inactive ingredients

alcohol denat., mineral oil, tridecyl salicylate, fragrance, acrylates/octylacrylamide copolymer, tocopheryl acetate, citrus sinensis (blood orange) oil, citrus aurantium dulcis (orange) peel oil, citrus aurantifolia (lime) oil